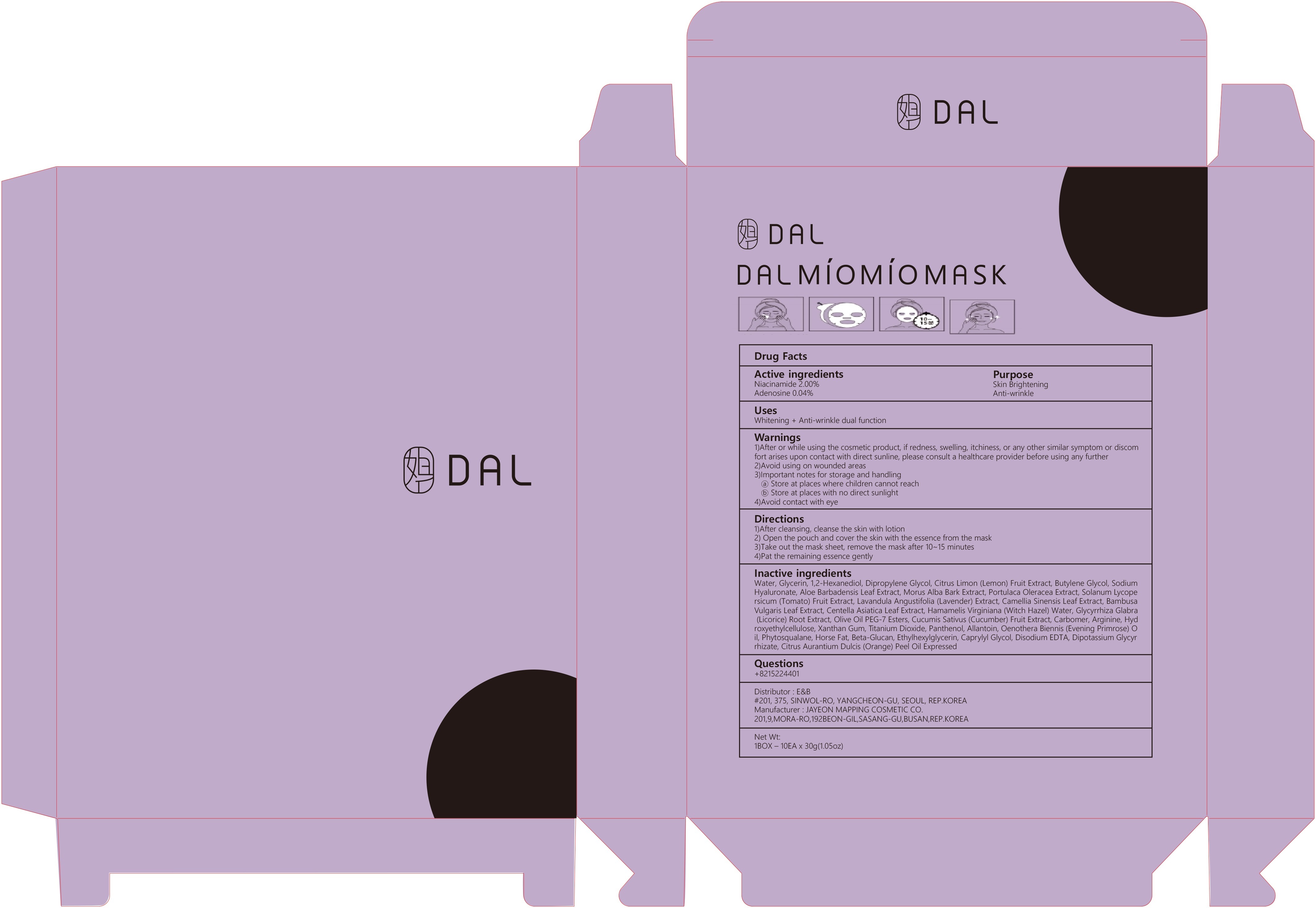 DRUG LABEL: DAL MIOMIO MASK
NDC: 73759-010 | Form: PATCH
Manufacturer: E&B
Category: otc | Type: HUMAN OTC DRUG LABEL
Date: 20200330

ACTIVE INGREDIENTS: Niacinamide 0.6 g/30 g; Adenosine 0.01 g/30 g
INACTIVE INGREDIENTS: Water; Glycerin; 1,2-Hexanediol

ACTIVE INGREDIENT

Active ingredients: Niacinamide 2.00%, Adenosine 0.04%

PURPOSE

Purpose: Skin Brightening, Anti-wrinkle

WARNINGS

1)After or while using the cosmetic product, if redness, swelling, itchiness, or any other similar symptom or discomfort arises upon contact with direct sunline, please consult a healthcare provider before using any further
2)Avoid using on wounded areas
3)Important notes for storage and handling
a) Store at places where children cannot reach
b) Store at places with no direct sunlight
4)Avoid contact with eye

KEEP OUT OF REACH OF CHILDREN

Uses

Uses: Whitening + Anti-wrinkle dual function

Directions

1)After cleansing, cleanse the skin with lotion
2) Open the pouch and cover the skin with the essence from the mask
3)Take out the mask sheet, remove the mask after 10~15 minutes
4)Pat the remaining essence gently

INACTIVE INGREDIENT

Inactive ingredients:

Water, Glycerin, 1,2-Hexanediol, Dipropylene Glycol, Citrus Limon (Lemon) Fruit Extract, Butylene Glycol, Sodium Hyaluronate, Aloe Barbadensis Leaf Extract, Morus Alba Bark Extract, Portulaca Oleracea Extract, Solanum Lycopersicum (Tomato) Fruit Extract, Lavandula Angustifolia (Lavender) Extract, Camellia Sinensis Leaf Extract, Bambusa Vulgaris Leaf Extract, Centella Asiatica Leaf Extract, Hamamelis Virginiana (Witch Hazel) Water, Glycyrrhiza Glabra (Licorice) Root Extract, Olive Oil PEG-7 Esters, Cucumis Sativus (Cucumber) Fruit Extract, Carbomer, Arginine, Hydroxyethylcellulose, Xanthan Gum, Titanium Dioxide, Panthenol, Allantoin, Oenothera Biennis (Evening Primrose) Oil, Phytosqualane, Horse Fat, Beta-Glucan, Ethylhexylglycerin, Caprylyl Glycol, Disodium EDTA, Dipotassium Glycyrrhizate, Citrus Aurantium Dulcis (Orange) Peel Oil Expressed